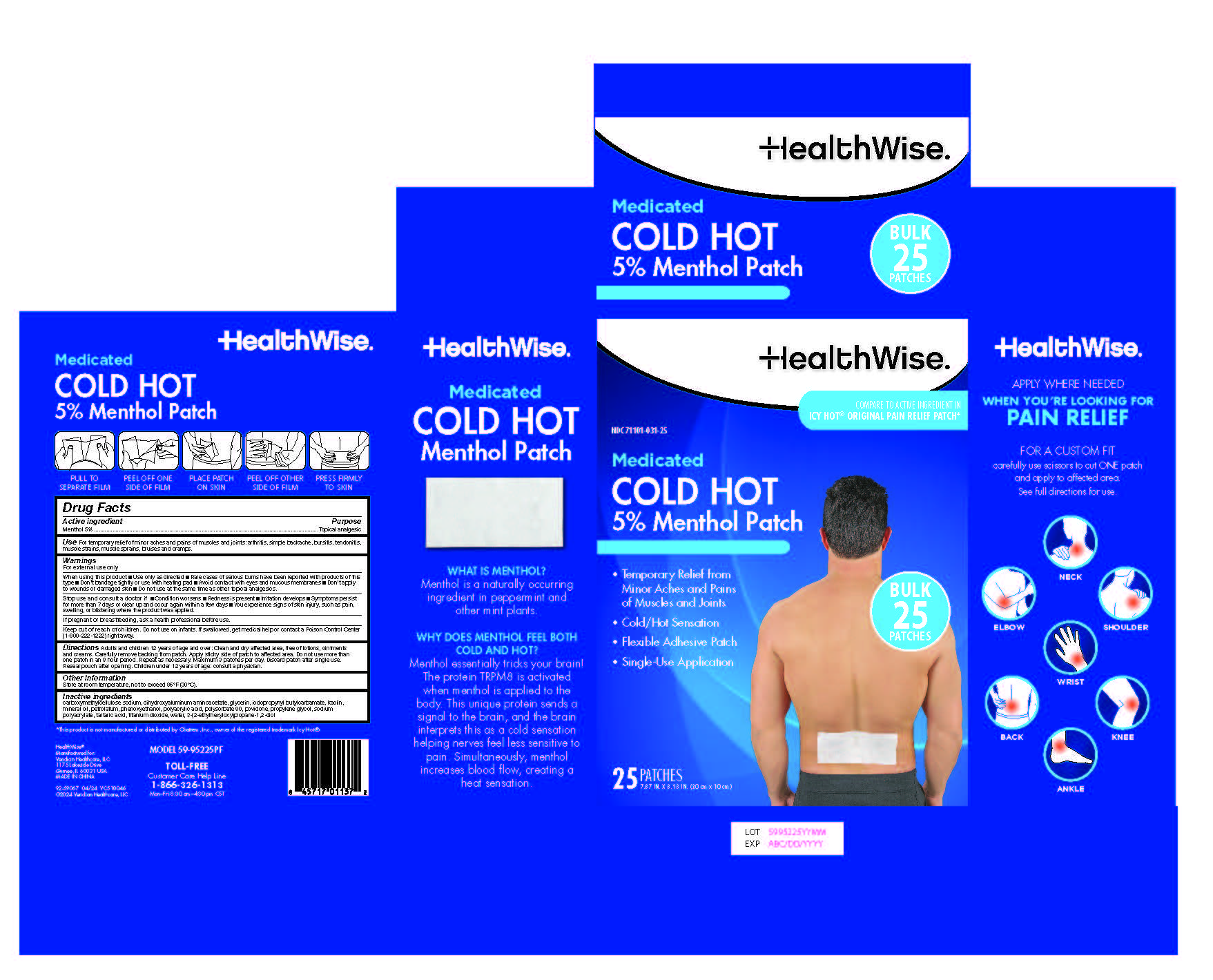 DRUG LABEL: HealthWise Medicated Cold Hot 5% Patch
NDC: 71101-031 | Form: PATCH
Manufacturer: Veridian Healthcare
Category: otc | Type: HUMAN OTC DRUG LABEL
Date: 20251023

ACTIVE INGREDIENTS: MENTHOL 5 g/1 1
INACTIVE INGREDIENTS: PETROLATUM; MINERAL OIL; WATER; GLYCERIN; SODIUM POLYACRYLATE (8000 MW); DIHYDROXYALUMINUM AMINOACETATE; ETHYLHEXYLGLYCERIN; PHENOXYETHANOL; TITANIUM DIOXIDE; KAOLIN; POLYSORBATE 80; PROPYLENE GLYCOL; CARBOXYMETHYLCELLULOSE SODIUM, UNSPECIFIED FORM; TARTARIC ACID; POVIDONE, UNSPECIFIED; POLYACRYLIC ACID (8000 MW); IODOPROPYNYL BUTYLCARBAMATE

HealthWise Medicated Cold Hot 5% Menthol Patch

ACTIVE INGREDIENT

Active Ingredient ...............................................................................................Purpose
Menthol 5%...............................................................................................Topical Analgesic

INACTIVE INGREDIENT

carboxymethylcellulose sodium, Dihydroxyaluminum Aminoacetate, Glycerin, iodopropynyl butylcarbamate, Kaolin, Mineral Oil, Petrolatum, Phenoxyethanol, Polyacrylic Acid, Polysorbate 80, povidone, Propylene Glycol, Sodium Polyacrylate, Tartaric Acid, Titanium Dioxide, Water, 3-(2-ethylhexyloxy)propane-1,2-diol

KEEP OUT OF REACH OF CHILDREN

Do not use on infants. If swallowed, get medical help or contact a Poison Control Center (1-800-222-1222) right away

INDICATIONS & USAGE

Temporarily relieves minor pain associated with: ■ arthritis ■ simple backache ■ bursitis ■ tendonitis
■ muscle strains ■ muscle sprains ■ bruises ■ cramps

WARNINGS

For External Use Only.

DOSAGE & ADMINISTRATION

Adults and children 12 years of age and over: Clean and dry affected area, free of lotions, ointments and creams. Carefully remove backing from patch. Apply sticky side of patch to affected area. Do not use more than one patch in an 8 hour period. Repeat as necessary. Maximum 3 patches per day. Discard patch after single use. Reseal pouch after opening.

Children under 12 years of age: consult a physician.

PURPOSE

Topical Analgesic

When using this product

■ Use only as directed

■ Rare cases of serious burns have been reported with products of this type

■Don't bandage tightly or use with heating pad

■ Avoid contact with eyes and mucous membranes

■ Don't apply to wounds or damaged skin

■ Do not use at the same time as other topical analgesics.

Stop use and ask a doctor

If condition worsens ■ If redness is present ■ If irritation develops
■ If symptoms persist for more than 7 days or clear up and occur again within a few days.

■ You experience signs injury, such a s pain, swelling, or blistering where the product was applied.

If pregnant or breastfeeding

ask a health professional before use.